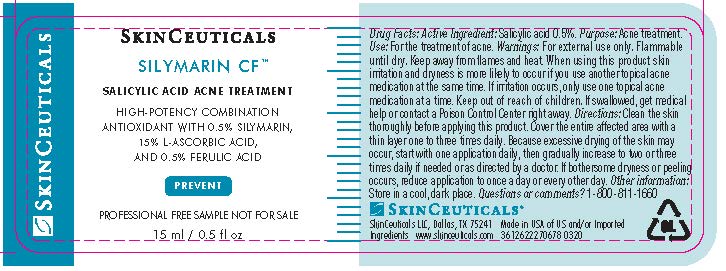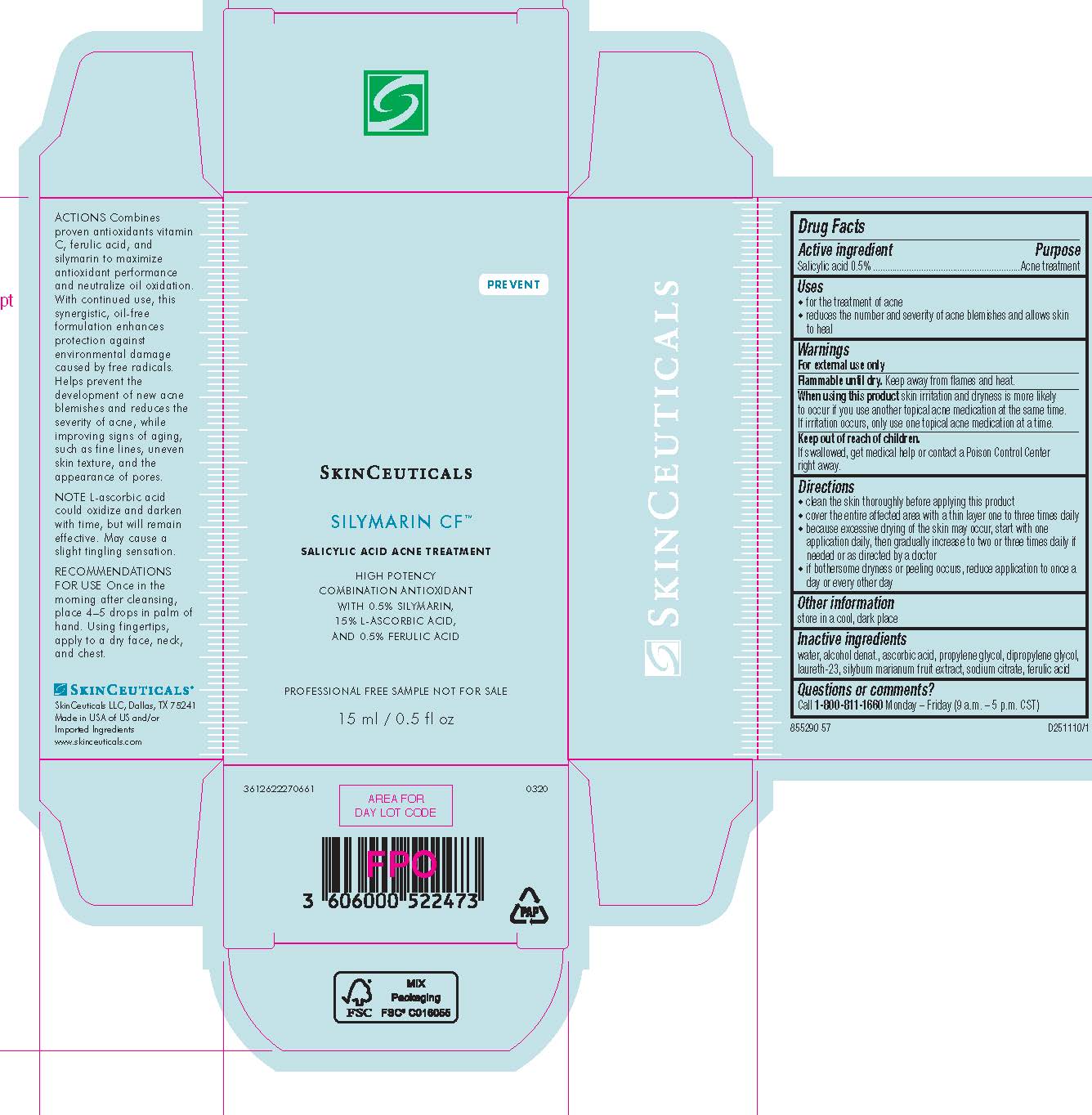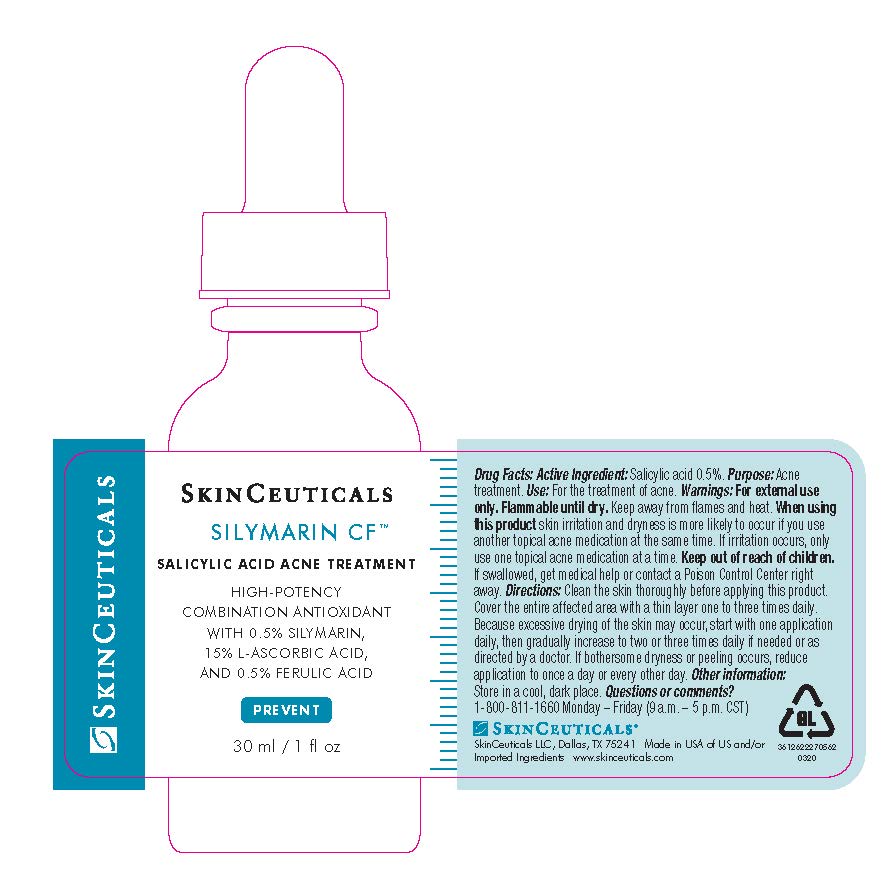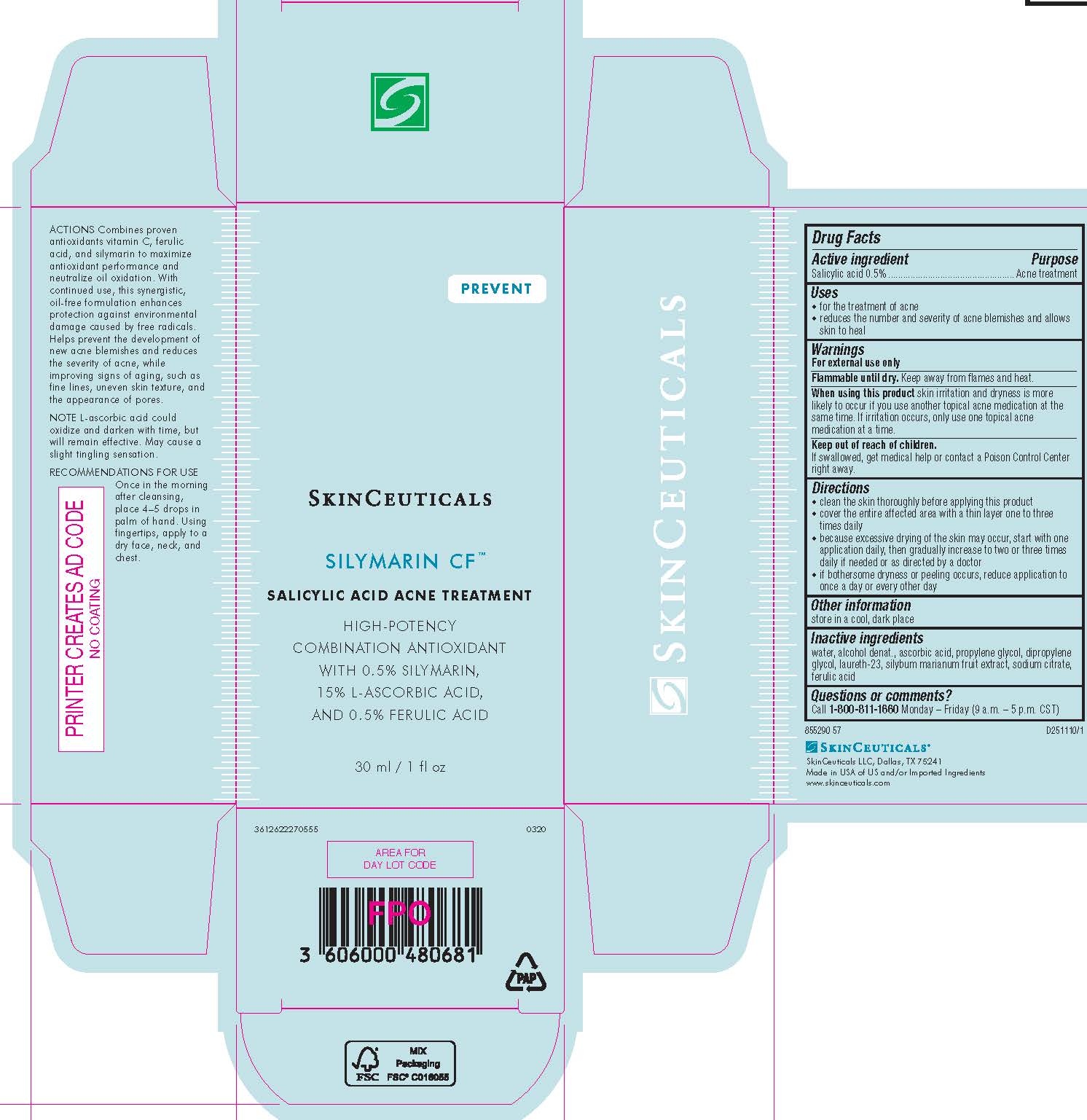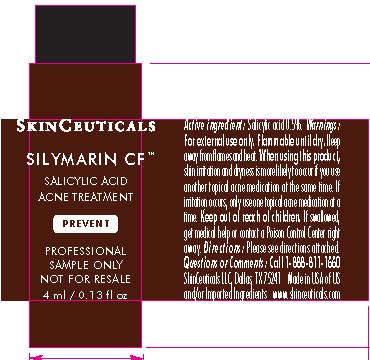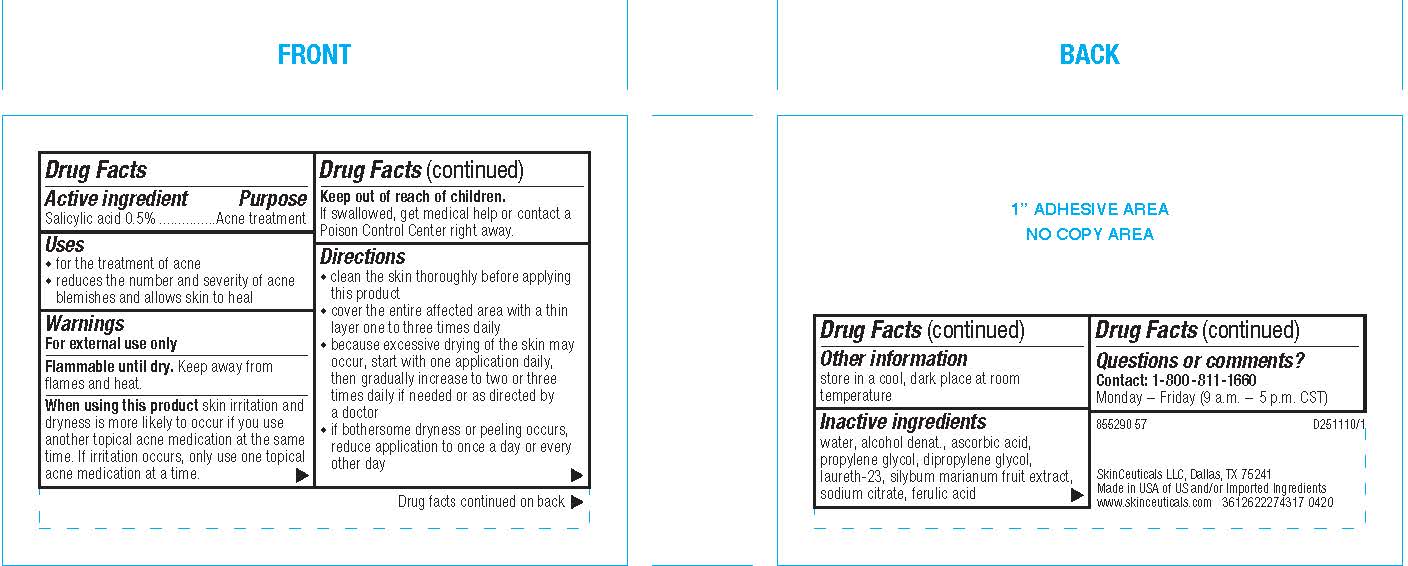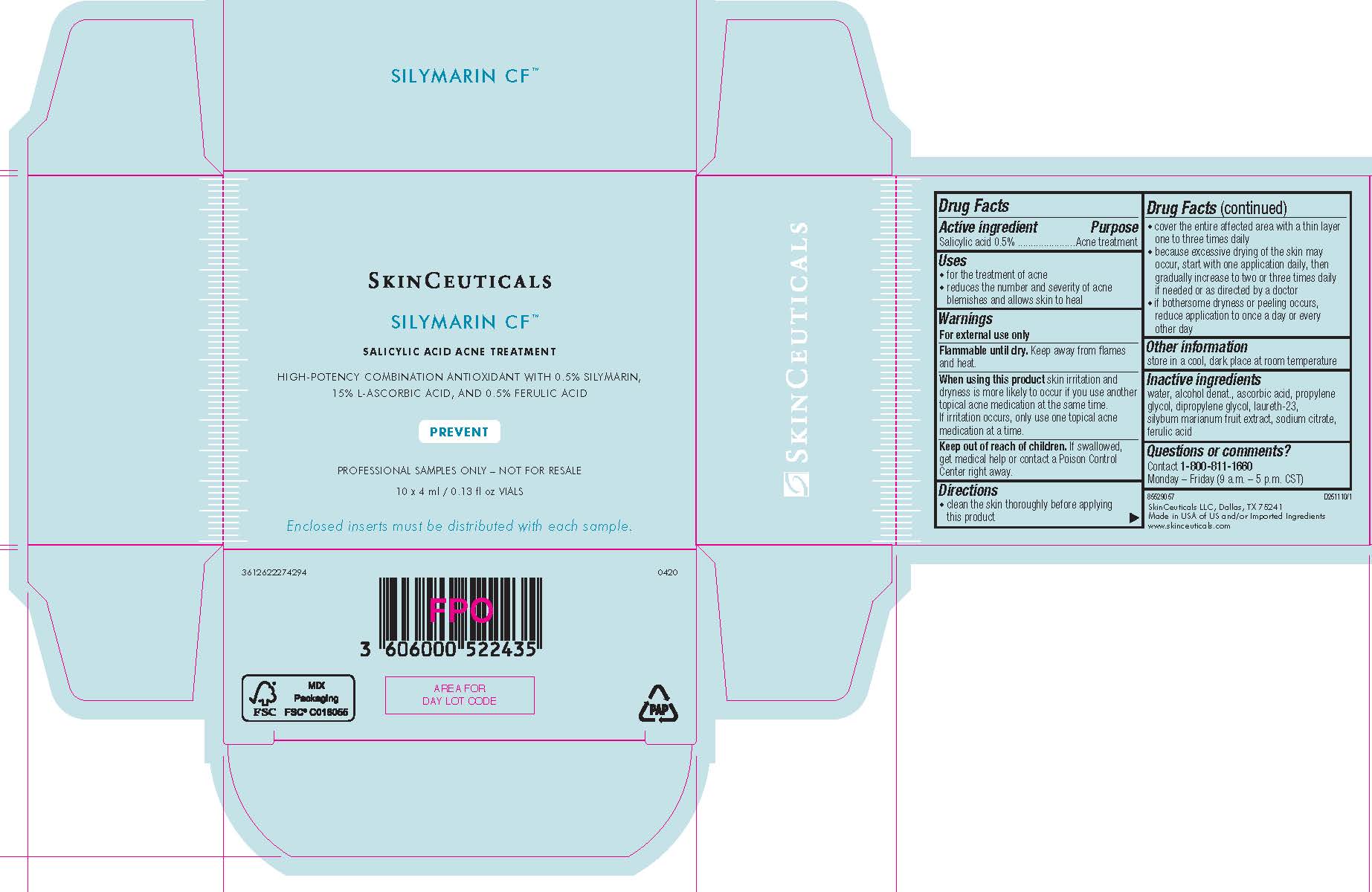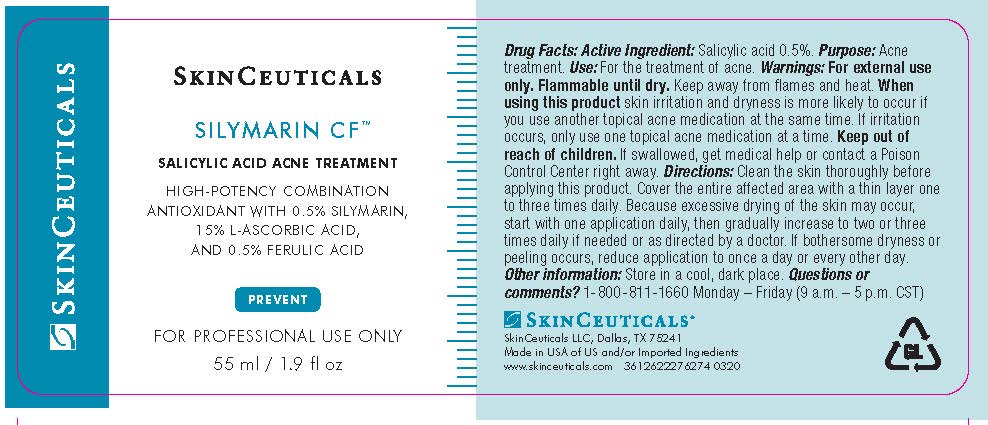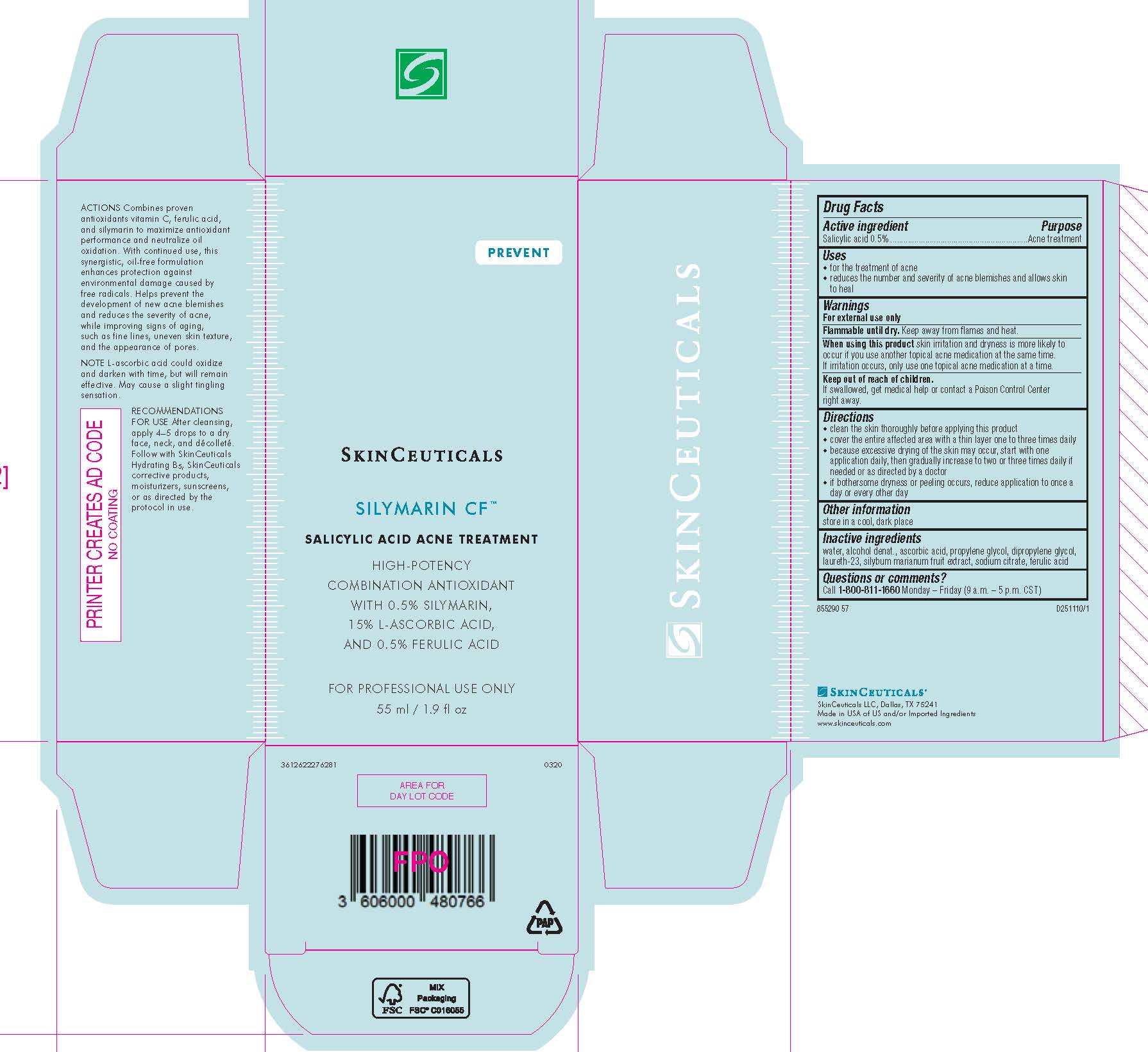 DRUG LABEL: SkinCeuticals Silymarin CF Acne Treatment Antioxidant
NDC: 69625-069 | Form: SOLUTION
Manufacturer: Cosmetique Active Production
Category: otc | Type: HUMAN OTC DRUG LABEL
Date: 20240624

ACTIVE INGREDIENTS: SALICYLIC ACID 5 mg/1 mL
INACTIVE INGREDIENTS: WATER; ALCOHOL; ASCORBIC ACID; PROPYLENE GLYCOL; DIPROPYLENE GLYCOL; LAURETH-23; MILK THISTLE; SODIUM CITRATE; FERULIC ACID

Drug Facts

Active ingredient

Salicylic acid 0.5%

Purpose

Acne treatment

Uses

- for the treatment of acne

- reduces the number and severity of acne blemishes and allows skin to heal

Warnings

For external use only

Flammable until dry.

Keep away from flames and heat.

When using this product

skin irritation and dryness is more liekly to occur if you use another topical acne medication at the same time. If irritation occurs, only use one topical acne medication at a time.

Keep out of reach of children.

If swallowed, get medical help or contact a Poison Control Center right away.

Directions

- clean the skin thoroughly before applying this product

- cover the entire affected area with a thin layer one to three times daily

- because excessive drying of the skin may occur, start with one application daily, then gradually increase to two or three times daily if needed or as directed by a doctor

- if bothersome dryness or peeling occurs, reduce application to once a day or every other day

Other information

store in a cool, dark place

Inactive ingredients

water, alcohol denat., ascorbic acid, propylene glycol, dipropylene glycol, laureth-23, silybum marianum fruit extract, sodium citrate, ferulic acid

Questions or comments?

Call 1-800-811-1660 Monday - Friday (9 a.m. - 5 p.m. CST)